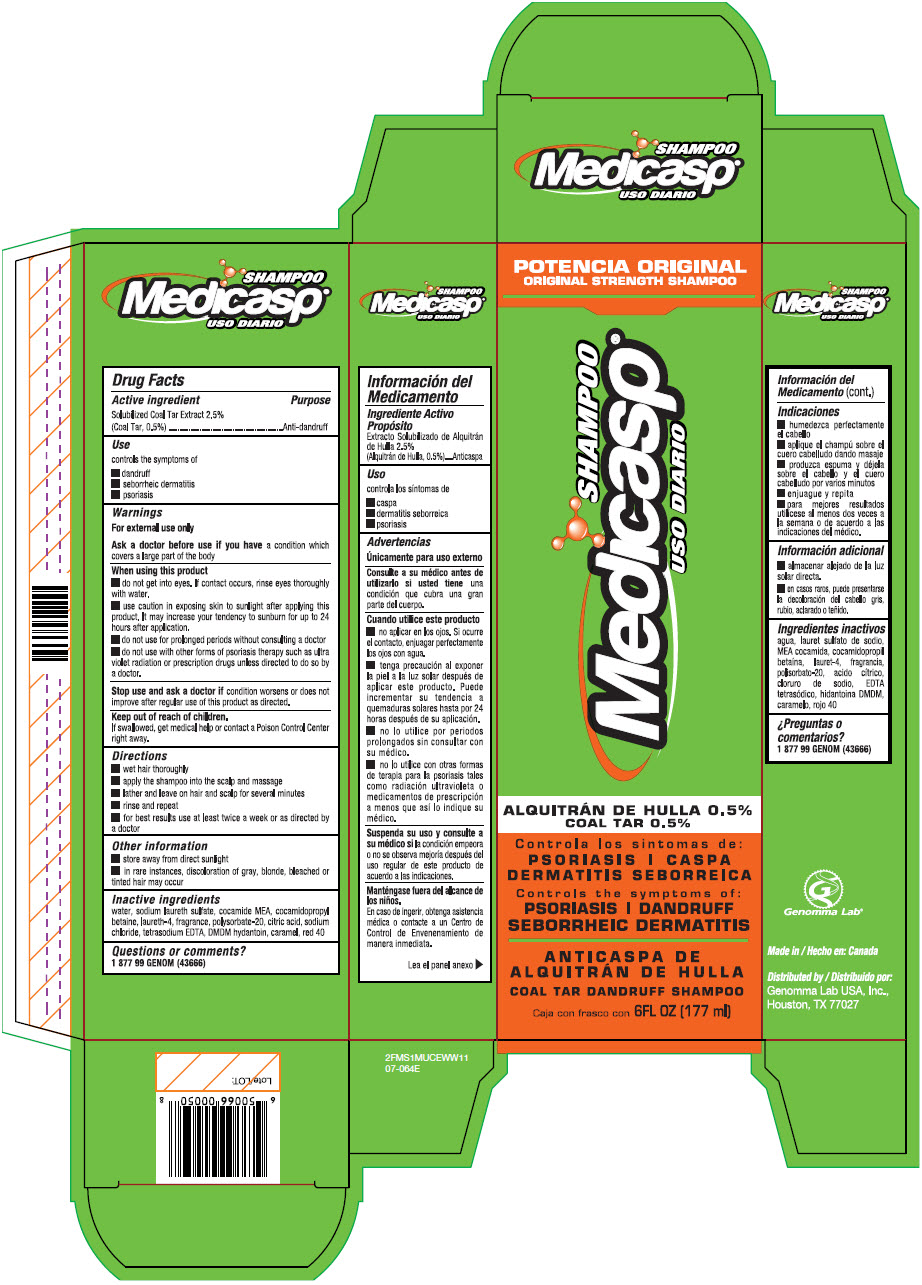 DRUG LABEL: Medicasp
NDC: 50066-054 | Form: SHAMPOO
Manufacturer: Genomma Lab USA Inc.
Category: otc | Type: HUMAN OTC DRUG LABEL
Date: 20241108

ACTIVE INGREDIENTS: Coal Tar 5 mg/1 mL
INACTIVE INGREDIENTS: Water; Sodium Laureth-3 Sulfate; COCO Monoethanolamide; Cocamidopropyl Betaine; Laureth-4; Polysorbate 20; Citric Acid Monohydrate; Sodium Chloride; Edetate Sodium; DMDM Hydantoin; Caramel; FD&C Red No. 40

Medicasp Shampoo®
Anti-dandruff

Drug Facts

Active ingredient

Solubilized Coal Tar Extract 2.5% (Coal Tar, 0.5%

Purpose

Anti-dandruff

Use

controls the symptoms of

- dandruff
- seborrheic dermatitis
- psoriasis

Warnings

For external use only

Ask a doctor before use if you have a condition which covers a large part of the body

When using this product

- do not get into the eyes. If contact occurs, rinse eyes thoroughly with water
- use caution exposing skin to sunlight after applying this product. It may increase your tendency to sunburn for up to 24 hours after application.
- do not use for prolonged periods without consulting a doctor
- do not use with other forms of psoriasis therapy such as ultra violet radiation or prescription drugs unless directed to do so by a doctor.

Stop use and ask a doctor if condition worsens or does not improve after regular use of this product as directed.

Keep out of reach of children.

If swallowed, get medical help or contact a Poison Control Center right away.

Directions

- wet hair thoroughly
- apply the shampoo into the scalp and massage
- lather and leave on hair and scalp for several minutes
- rinse and repeat
- for best results use at least twice a week or as directed by a doctor

Other information

- store away from direct sunlight
- in rare instances, discoloration of gray, blonde, bleached or tinted hair may occur

Inactive ingredients

water, sodium laureth sulfate, cocamide MEA, cocamidopropyl betaine, laureth-4, fragrance, polysorbate 20, citric acid, sodium chloride, tetrasodium EDTA, DMDM hydantoin, caramel, red 40

Questions or comments?

1 877 99 GENOM (43666)

Distributed by:
Genomma Lab USA, Inc.,
Houston, TX 77027

PRINCIPAL DISPLAY PANEL - 177 ml Bottle Carton

ORIGINAL STRENGTH SHAMPOO

SHAMPOO
Medicasp®

COAL TAR 0.5%

Controls the symptoms of:
PSORIASIS | DANDRUFF
SEBORRHEIC DERMATITIS

COAL TAR DANDRUFF SHAMPOO

6FL OZ (177 ml)